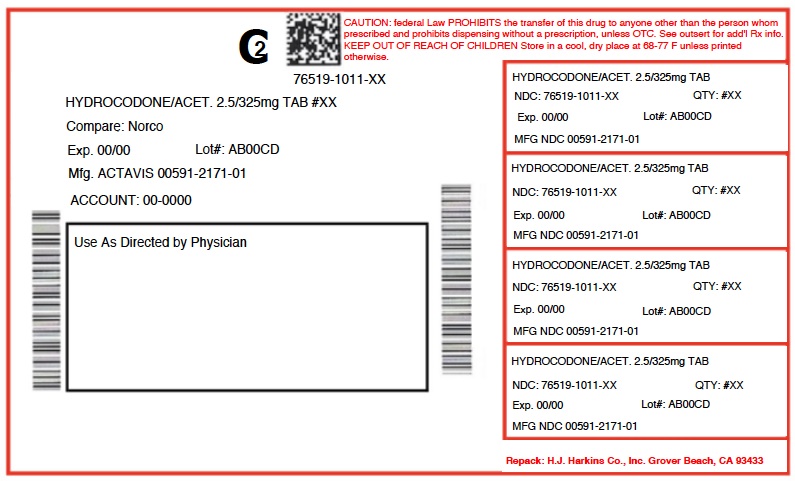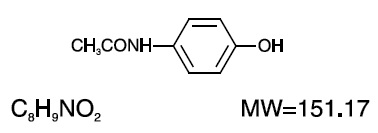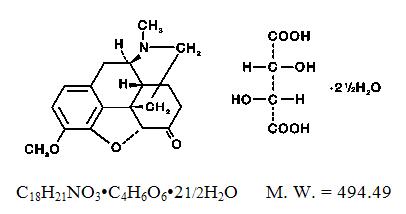 DRUG LABEL: Hydrocodone Bitartate and Acetaminophen
NDC: 76519-1011 | Form: TABLET
Manufacturer: H.J. Harkins Company, Inc.
Category: prescription | Type: HUMAN PRESCRIPTION DRUG LABEL
Date: 20180926
DEA Schedule: CII

ACTIVE INGREDIENTS: HYDROCODONE BITARTRATE 2.5 mg/1 1; ACETAMINOPHEN 325 mg/1 1

1011 HYDRO/APAP 2.5/325MG

BOXED WARNING

WARNING: ADDICTION, ABUSE, AND MISUSE; LIFE-THREATENING RESPIRATORY DEPRESSION; ACCIDENTAL INGESTION; NEONATAL OPIOID WITHDRAWAL SYNDROME; CYTOCHROME P450 3A4 INTERACTION and HEPATOTOXICITY

Addiction, Abuse, and Misuse
Hydrocodone bitartrate and acetaminophen tablets exposes patients and other users to the risks of opioid addiction, abuse, and misuse, which can lead to overdose and death. Assess each patient’s risk prior to prescribing hydrocodone bitartrate and acetaminophen tablets, and monitor all patients regularly for the development of these behaviors or conditions [see WARNINGS].

Life-Threatening Respiratory Depression
Serious, life-threatening, or fatal respiratory depression may occur with use of hydrocodone bitartrate and acetaminophen tablets. Monitor for respiratory depression, especially during initiation of hydrocodone bitartrate and acetaminophen tablets or following a dose increase [see WARNINGS].

Accidental Ingestion
Accidental ingestion of even one dose of hydrocodone bitartrate and acetaminophen tablets, especially by children, can result in a fatal overdose of hydrocodone bitartrate and acetaminophen tablets [see WARNINGS].

Neonatal Opioid Withdrawal Syndrome
Prolonged use of hydrocodone bitartrate and acetaminophen tablets during pregnancy can result in neonatal opioid withdrawal syndrome, which may be life-threatening if not recognized and treated, and requires management according to protocols developed by neonatology experts. If opioid use is required for a prolonged period in a pregnant woman, advise the patient of the risk of neonatal opioid withdrawal syndrome and ensure that appropriate treatment will be available [see WARNINGS].

Cytochrome P450 3A4 Interaction
The concomitant use of hydrocodone bitartrate and acetaminophen tablets with all cytochrome P450 3A4 inhibitors may result in an increase in hydrocodone bitartrate and acetaminophen tabletsplasma concentrations, which could increase or prolong adverse reactions and may cause potentially fatal respiratory depression. In addition, discontinuation of a concomitantly used cytochrome P450 3A4 inducer may result in an increase in hydrocodone bitartrate and acetaminophen tablets plasma concentration. Monitor patients receiving hydrocodone bitartrate and acetaminophen tabletsand any CYP3A4 inhibitor or inducer [see CLINICAL PHARMACOLOGY, WARNINGS, PRECAUTIONS; Drug Interactions].

Hepatotoxicity
Acetaminophen has been associated with cases of acute liver failure, at times resulting in liver transplant and death. Most of the cases of liver injury are associated with the use of acetaminophen at doses that exceed 4000 milligrams per day, and often involve more than one acetaminophen containing product.

DESCRIPTION

Hydrocodone bitartrate and acetaminophen is supplied in tablet form for oral administration.

Hydrocodone bitartrate is an opioid analgesic and antitussive and occurs as fine, white crystals or as a crystalline powder. It is affected by light. The chemical name is 4,5α-Epoxy-3-methoxy-17-methylmorphinan-6-one tartrate (1:1) hydrate (2:5). It has the following structural formula:

Acetaminophen, 4´-Hydroxyacetanilide, a slightly bitter, white, odorless, crystalline powder, is a non-opiate, non-salicylate analgesic and antipyretic. It has the following structural formula:

Hydrocodone Bitartrate and Acetaminophen Tablets, USP for oral administration are available in a variety of strengths as described in the following table.

Hydrocodone
Strength Bitartrate Acetaminophen

2.5 mg/325 mg 2.5 mg 325 mg
5 mg/325 mg 5 mg 325 mg

7.5 mg/325 mg 7.5 mg 325 mg

10 mg/325 mg 10 mg 325 mg

In addition, each tablet contains the following inactive ingredients: microcrystalline cellulose, croscarmellose sodium and magnesium stearate. Meets USP Dissolution Test 1.

CLINICAL PHARMACOLOGY

Hydrocodone is a semisynthetic narcotic analgesic and antitussive with multiple actions qualitatively similar to those of codeine. Most of these involve the central nervous system and smooth muscle. The precise mechanism of action of hydrocodone and other opiates is not known, although it is believed to relate to the existence of opiate receptors in the central nervous system. In addition to analgesia, narcotics may produce drowsiness, changes in mood and mental clouding.

The analgesic action of acetaminophen involves peripheral influences, but the specific mechanism is as yet undetermined. Antipyretic activity is mediated through hypothalamic heat regulating centers. Acetaminophen inhibits prostaglandin synthetase. Therapeutic doses of acetaminophen have negligible effects on the cardiovascular or respiratory systems; however, toxic doses may cause circulatory failure and rapid, shallow breathing.

Pharmacokinetics:

The behavior of the individual components is described below.

Hydrocodone: Following a 10 mg oral dose of hydrocodone administered to five adult male subjects, the mean peak concentration was 23.6 ± 5.2 ng/mL. Maximum serum levels were achieved at 1.3 ± 0.3 hours and the half-life was determined to be 3.8 ± 0.3 hours. Hydrocodone exhibits a complex pattern of metabolism including O-demethylation, N-demethylation and 6-ketoreduction to the corresponding 6-α- and 6-β-hydroxymetabolites. See OVERDOSAGE for toxicity information.

Acetaminophen: Acetaminophen is rapidly absorbed from the gastrointestinal tract and is distributed throughout most body tissues. The plasma half-life is 1.25 to 3 hours, but may be increased by liver damage and following overdosage. Elimination of acetaminophen is principally by liver metabolism (conjugation) and subsequent renal excretion of metabolites. Approximately 85% of an oral dose appears in the urine within 24 hours of administration, most as the glucuronide conjugate, with small amounts of other conjugates and unchanged drug. See OVERDOSAGE for toxicity information.

INDICATIONS AND USAGE

Hydrocodone bitartrate and acetaminophen tablets are indicated for the management of moderate to moderately severe pain severe enough to require an opioid analgesic and for which alternative treatments are inadequate.

Limitations of Use
Because of the risks of addiction, abuse, and misuse, with opioids, even at recommended doses [seeWARNINGS], reserve hydrocodone bitartrate and acetaminophen tablets for use in patients for whom alternative treatment options [e.g., non-opioid analgesics]

Have not been tolerated, or are not expected to be tolerated,
Have not provided adequate analgesia, or are not expected to provide adequate analgesia

CONTRAINDICATIONS

Hydrocodone bitartrate and acetaminophen tablets are contraindicated in patients with:

Significant respiratory depression [see WARNINGS]
Acute or severe bronchial asthma in an unmonitored setting or in the absence of resuscitative equipment [see WARNINGS]
Patients who have previously exhibited hypersensitivity to hydrocodone or acetaminophen.
Known hypersensitivity to other opioids who may exhibit cross-sensitivity to hydrocodone.

WARNINGS

Addiction, Abuse, and Misuse

Hydrocodone bitartrate and acetaminophen tablet contains hydrocodone a Schedule II controlled substance. As an opioid, hydrocodone bitartrate and acetaminophen tablets expose users to the risks of addiction, abuse, and misuse [see DRUG ABUSE AND DEPENDENCE].

Although the risk of addiction in any individual is unknown, it can occur in patients appropriately prescribed hydrocodone bitartrate and acetaminophen tablets. Addiction can occur at recommended dosages and if the drug is misused or abused.

Assess each patient’s risk for opioid addiction, abuse, or misuse prior to prescribing hydrocodone bitartrate and acetaminophen tablets, and monitor all patients receiving hydrocodone bitartrate and acetaminophen tablets for the development of these behaviors or conditions. Risks are increased in patients with a personal or family history of substance abuse (including drug or alcohol abuse or addiction) or mental illness (e.g., major depression). The potential for these risks should not, however, prevent the proper management of pain in any given patient. Patients at increased risk may be prescribed opioids such as hydrocodone bitartrate and acetaminophen tablets, but use in such patients necessitates intensive counseling about the risks and proper use of hydrocodone bitartrate and acetaminophen tablet along with intensive monitoring for signs of addiction, abuse, and misuse.

Opioids are sought by drug abusers and people with addiction disorders and are subject to criminal diversion. Consider these risks when prescribing or dispensing hydrocodone bitartrate and acetaminophen tablets. Strategies to reduce these risks include prescribing the drug in the smallest appropriate quantity and advising the patient on the proper disposal of unused drug [seePRECAUTIONS; INFORMATION FOR PATIENTS]. Contact local state professional licensing board or state controlled substances authority for information on how to prevent and detect abuse or diversion of this product.

Life-Threatening Respiratory Depression

Serious, life-threatening, or fatal respiratory depression has been reported with the use of opioids, even when used as recommended. Respiratory depression, if not immediately recognized and treated, may lead to respiratory arrest and death. Management of respiratory depression may include close observation, supportive measures, and use of opioid antagonists, depending on the patient’s clinical status [see OVERDOSAGE]. Carbon dioxide (CO2) retention from opioid-induced respiratory depression can exacerbate the sedating effects of opioids. While serious, life-threatening, or fatal respiratory depression can occur at any time during the use of hydrocodone bitartrate and acetaminophen tablets, the risk is greatest during the initiation of therapy or following a dosage increase. Monitor patients closely for respiratory depression, especially within the first 24-72 hours of initiating therapy with and following dosage increases of hydrocodone bitartrate and acetaminophen tablets.

To reduce the risk of respiratory depression, proper dosing and titration of hydrocodone bitartrate and acetaminophen tablets are essential [see DOSAGE AND ADMINISTRATION]. Overestimating the hydrocodone bitartrate and acetaminophen tablets dosage when converting patients from another opioid product can result in a fatal overdose with the first dose.

Accidental ingestion of even one dose of hydrocodone bitartrate and acetaminophen tablets, especially by children, can result in respiratory depression and death due to an overdose of hydrocodone.

Neonatal Opioid Withdrawal Syndrome

Prolonged use of hydrocodone bitartrate and acetaminophen tablets during pregnancy can result in withdrawal in the neonate. Neonatal opioid withdrawal syndrome unlike opioid withdrawal syndrome in adults, may be life-threatening if not recognized and treated, and requires management according to protocols developed by neonatology experts. If opioid use is required for a prolonged period in a pregnant woman, advise the patient of the risk of neonatal opioid withdrawal syndrome and ensure that appropriate treatment will be available [see PRECAUTIONS; INFORMATION FOR PATIENTS,PREGNANCY].

Hepatotoxicity

Acetaminophen has been associated with cases of acute liver failure, at times resulting in liver transplant and death. Most of the cases of liver injury are associated with the use of acetaminophen at doses that exceed 4000 milligrams per day, and often involve more than one acetaminophen containing product. The excessive intake of acetaminophen may be intentional to cause self-harm or unintentional as patients attempt to obtain more pain relief or unknowingly take other acetaminophen-containing products.

The risk of acute liver failure is higher in individuals with underlying liver disease and in individuals who ingest alcohol while taking acetaminophen.

Instruct patients to look for acetaminophen or APAP on package labels and not to use more than one product that contains acetaminophen. Instruct patients to seek medical attention immediately upon ingestion of more than 4000 milligrams of acetaminophen per day, even if they feel well.

Serious skin reactions

Rarely, acetaminophen may cause serious skin reactions such as acute generalized exanthematous pustulosis (AGEP), Stevens-Johnson Syndrome (SJS), and toxic epidermal necrolysis (TEN), which can be fatal. Patients should be informed about the signs of serious skin reactions, and use of the drug should be discontinued at the first appearance of skin rash or any other sign of hypersensitivity.

Hypersensitivity/anaphylaxis

There have been post-marketing reports of hypersensitivity and anaphylaxis associated with use of acetaminophen. Clinical signs included swelling of the face, mouth, and throat, respiratory distress, urticaria, rash, pruritus, and vomiting. There were infrequent reports of life-threatening anaphylaxis requiring emergency medical attention. Instruct patients to discontinue Hydrocodone Bitartrate and Acetaminophen Tablets, USP immediately and seek medical care if they experience these symptoms. Do not prescribe Hydrocodone Bitartrate and Acetaminophen Tablets, USP for patients with acetaminophen allergy.

Head Injury and Increased Intracranial Pressure:

The respiratory depressant effects of narcotics and their capacity to elevate cerebrospinal fluid pressure may be markedly exaggerated in the presence of head injury, other intracranial lesions or a pre-existing increase in intracranial pressure. Furthermore, narcotics produce adverse reactions which may obscure the clinical course of patients with head injuries.

Acute Abdominal Conditions:

The administration of narcotics may obscure the diagnosis or clinical course of patients with acute abdominal conditions.

Risks of Concomitant Use or Discontinuation of Cytochrome P450 3A4 Inhibitors and Inducers

Concomitant use of hydrocodone bitartrate and acetaminophen tablets with a CYP3A4 inhibitor, such as macrolide antibiotics (e.g., erythromycin), azole-antifungal agents (e.g., ketoconazole), and protease inhibitors (e.g., ritonavir), may increase plasma concentrations of hydrocodone bitartrate and acetaminophen tablets and prolong opioid adverse reactions, which may cause potentially fatal respiratory depression [see WARNINGS], particularly when an inhibitor is added after a stable dose of hydrocodone bitartrate and acetaminophen tablets is achieved. Similarly, discontinuation of a CYP3A4 inducer, such as rifampin, carbamazepine, and phenytoin, in hydrocodone bitartrate and acetaminophen tablet-treated patients may increase hydrocodone bitartrate and acetaminophen tablets plasma concentrations and prolong opioid adverse reactions. When using hydrocodone bitartrate and acetaminophen tablets with CYP3A4 inhibitors or discontinuing CYP3A4 inducers in hydrocodone bitartrate and acetaminophen tablet-treated patients, monitor patients closely at frequent intervals and consider dosage reduction of hydrocodone bitartrate and acetaminophen tablets until stable drug effects are achieved [see PRECAUTIONS; DRUG INTERACTIONS].

Concomitant use of hydrocodone bitartrate and acetaminophen tablets with CYP3A4 inducers or discontinuation of an CYP3A4 inhibitor could decrease hydrocodone bitartrate and acetaminophen tablets plasma concentrations, decrease opioid efficacy or, possibly, lead to a withdrawal syndrome in a patient who had developed physical dependence to hydrocodone bitartrate and acetaminophen tablets. When using hydrocodone bitartrate and acetaminophen tablets with CYP3A4 inducers or discontinuing CYP3A4 inhibitors, monitor patients closely at frequent intervals and consider increasing the opioid dosage if needed to maintain adequate analgesia or if symptoms of opioid withdrawal occur [seePRECAUTIONS; DRUG INTERACTIONS].

Risks due to Interactions with Central Nervous System Depressants

Hypotension, profound sedation, respiratory depression, coma, and death may result if hydrocodone bitartrate and acetaminophen tablets are used concomitantly with alcohol or other central nervous system (CNS) depressants (e.g., benzodiazepines and other sedatives/hypnotics, anxiolytics, and tranquilizers, muscle relaxants, general anesthetics, antipsychotics, other opioids).

When considering the use of hydrocodone bitartrate and acetaminophen tablets in a patient taking a CNS depressant, assess the duration of use of the CNS depressant and the patient’s response, including the degree of tolerance that has developed to CNS depression. Additionally, evaluate the patient’s use of alcohol or illicit drugs that can cause CNS depression. If the decision to begin hydrocodone bitartrate and acetaminophen tablets is made, start with a lower dosage of hydrocodone bitartrate and acetaminophen tablets, monitor patients for signs of respiratory depression, sedation, and hypotension, and consider using a lower dose of the concomitant CNS depressant [see PRECAUTIONS; DRUG INTERACTIONS].

Life-Threatening Respiratory Depression in Patients with Chronic Pulmonary Disease or in Elderly, Cachectic, or Debilitated Patients

The use of hydrocodone bitartrate and acetaminophen tablets in patients with acute or severe bronchial asthma in an unmonitored setting or in the absence of resuscitative equipment is contraindicated.

Patients with Chronic Pulmonary Disease: Hydrocodone bitartrate and acetaminophen tablet-treated patients with significant chronic obstructive pulmonary disease or cor pulmonale, and those with a substantially decreased respiratory reserve, hypoxia, hypercapnia, or pre-existing respiratory depression are at increased risk of decreased respiratory drive including apnea, even at recommended dosages of hydrocodone bitartrate and acetaminophen tablets [see WARNINGS].

Elderly, Cachectic, or Debilitated Patients: Life-threatening respiratory depression is more likely to occur in elderly, cachectic, or debilitated patients because they may have altered pharmacokinetics or altered clearance compared to younger, healthier patients [see WARNINGS].

Monitor such patients closely, particularly when initiating and titrating hydrocodone bitartrate and acetaminophen tablets and when hydrocodone bitartrate and acetaminophen tablets are given concomitantly with other drugs that depress respiration [see WARNINGS]. Alternatively, consider the use of non-opioid analgesics in these patients.

Adrenal Insufficiency

Cases of adrenal insufficiency have been reported with opioid use, more often following greater than 1 month of use. Presentation of adrenal insufficiency may include non-specific symptoms and signs including nausea, vomiting, anorexia, fatigue, weakness, dizziness, and low blood pressure. If adrenal insufficiency is suspected, confirm the diagnosis with diagnostic testing as soon as possible. If adrenal insufficiency is diagnosed, treat with physiologic replacement doses of corticosteroids. Wean the patient off of the opioid to allow adrenal function to recover and continue corticosteroid treatment until adrenal function recovers. Other opioids may be tried as some cases reported use of a different opioid without recurrence of adrenal insufficiency. The information available does not identify any particular opioids as being more likely to be associated with adrenal insufficiency.

PRECAUTIONS

General: Special Risk Patients: As with any narcotic analgesic agent, hydrocodone bitartrate and acetaminophen tablets should be used with caution in elderly or debilitated patients, and those with severe impairment of hepatic or renal function, hypothyroidism, Addison's disease, prostatic hypertrophy or urethral stricture. The usual precautions should be observed and the possibility of respiratory depression should be kept in mind.

Cough Reflex: Hydrocodone suppresses the cough reflex; as with all narcotics, caution should be exercised when hydrocodone bitartrate and acetaminophen tablets are used postoperatively and in patients with pulmonary disease.

Information for Patients/Caregivers

Do not take Hydrocodone Bitartrate and Acetaminophen Tablets, USP if you are allergic to any of its ingredients.
If you develop signs of allergy such as a rash or difficulty breathing stop taking Hydrocodone Bitartrate and Acetaminophen Tablets, USP and contact your healthcare provider immediately.
Do not take more than 4000 milligrams of acetaminophen per day. Call your doctor if you took more than the recommended dose.

Addiction, Abuse, and Misuse
Inform patients that the use of hydrocodone bitartrate and acetaminophen tablets, even when taken as recommended, can result in addiction, abuse, and misuse, which can lead to overdose and death [seeWARNINGS]. Instruct patients not to share hydrocodone bitartrate and acetaminophen tablets with others and to take steps to protect hydrocodone bitartrate and acetaminophen tablets from theft or misuse.

Life-Threatening Respiratory Depression
Inform patients of the risk of life-threatening respiratory depression, including information that the risk is greatest when starting hydrocodone bitartrate and acetaminophen tablets or when the dosage is increased, and that it can occur even at recommended dosages [see WARNINGS]. Advise patients how to recognize respiratory depression and to seek medical attention if breathing difficulties develop.

Accidental Ingestion
Inform patients that accidental ingestion, especially by children, may result in respiratory depression or death [see WARNINGS]. Instruct patients to take steps to store hydrocodone bitartrate and acetaminophen tablets securely and to dispose of unused hydrocodone bitartrate and acetaminophen tablets by flushing any unused tablets down the toilet.

Interactions with Alcohol and Other CNS Depressants
Inform patients that potentially serious additive effects may occur if hydrocodone bitartrate and acetaminophen tablets are used with alcohol or other CNS depressants and not to use such drugs unless supervised by a health care provider [see WARNINGS, PRECAUTIONS; DRUG INTERACTIONS].

Serotonin Syndrome
Inform patients that hydrocodone bitartrate and acetaminophen tablets could cause a rare but potentially life-threatening condition resulting from concomitant administration of serotonergic drugs. Warn patients of the symptoms of serotonin syndrome and to seek medical attention right away if symptoms develop. Instruct patients to inform their physicians if they are taking, or plan to take serotonergic medications [see PRECAUTIONS; DRUG INTERACTIONS].

Adrenal Insufficiency
Inform patients that hydrocodone bitartrate and acetaminophen tablets could cause adrenal insufficiency, a potentially lifethreatening condition. Adrenal insufficiency may present with non-specific symptoms and signs such as nausea, vomiting, anorexia, fatigue, weakness, dizziness, and low blood pressure. Advise patients to seek medical attention if they experience a constellation of these symptoms [see WARNINGS].

Pregnancy
Neonatal Opioid Withdrawal Syndrome
Inform patients that prolonged use of hydrocodone bitartrate and acetaminophen tablets during pregnancy can result in neonatal opioid withdrawal syndrome, which may be life-threatening if not recognized and treated [see WARNINGS, PRECAUTIONS; PREGNANCY]

Embryo-Fetal Toxicity
Inform female patients of reproductive potential that hydrocodone bitartrate and acetaminophen tablets can cause fetal harm and to inform the prescriber of a known or suspected pregnancy [seePRECAUTIONS; PREGNANCY].

Lactation
Advise nursing mothers to monitor infants for increased sleepiness (more than usual), breathing difficulties, or limpness. Instruct nursing mothers to seek immediate medical care if they notice these signs [see PRECAUTIONS; NURSING MOTHERS].

Disposal of Unused Hydrocodone Bitartrate and Acetaminophen Tablets
Advise patients to flush any unused tablets down the toilet.

Laboratory Tests: In patients with severe hepatic or renal disease, effects of therapy should be monitored with serial liver and/or renal function tests.

Drug Interactions: Patients receiving narcotics, antihistamines, antipsychotics, antianxiety agents, or other CNS depressants (including alcohol) concomitantly with hydrocodone bitartrate and acetaminophen tablets may exhibit an additive CNS depression. When combined therapy is contemplated, the dose of one or both agents should be reduced.

The use of MAO inhibitors or tricyclic antidepressants with hydrocodone preparations may increase the effect of either the antidepressant or hydrocodone.

CYP3A4
Inhibitor
The concomitant use of hydrocodone bitartrate and acetaminophen tablets and CYP3A4 inhibitors, such as macrolide antibiotics (e.g., erythromycin), azole-antifungal agents (e.g. ketoconazole), and protease inhibitors (e.g., ritonavir), can increase the plasma concentration of hydrocodone bitartrate and acetaminophen tablets, resulting in increased or prolonged opioid effects. These effects could be more pronounced with concomitant use of hydrocodone bitartrate and acetaminophen tablets and CYP3A4 inhibitors, particularly when an inhibitor is added after a stable dose of hydrocodone bitartrate and acetaminophen tablets is achieved [see WARNINGS].

After stopping a CYP3A4 inhibitor, as the effects of the inhibitor decline, the hydrocodone bitartrate and acetaminophen plasma concentration will decrease [see CLINICAL PHARMACOLOGY], resulting in decreased opioid efficacy or a withdrawal syndrome in patients who had developed physical dependence to hydrocodone bitartrate and acetaminophen tablets.

If concomitant use is necessary, consider dosage reduction of hydrocodone bitartrate and acetaminophen tablets until stable drug effects are achieved. Monitor patients for respiratory depression and sedation at frequent intervals. If a CYP3A4 inhibitor is discontinued, consider increasing the hydrocodone bitartrate and acetaminophen tablets dosage until stable drug effects are achieved [see DOSAGE AND ADMINISTRATION]. Monitor for signs of opioid withdrawal.

Inducer
The concomitant use of hydrocodone bitartrate and acetaminophen tablets and CYP3A4 inducers, such as rifampin, carbamazepine, and phenytoin, can decrease the plasma concentration of hydrocodone bitartrate and acetaminophen tablets [see CLINICAL PHARMACOLOGY], resulting in decreased efficacy or onset of a withdrawal syndrome in patients who have developed physical dependence to hydrocodone bitartrate and acetaminophen tablets [see WARNINGS].

After stopping a CYP3A4 inducer, as the effects of the inducer decline, the hydrocodone bitartrate and acetaminophen tablets plasma concentration will increase [see CLINICAL PHARMACOLOGY], which could increase or prolong both the therapeutic effects and adverse reactions, and may cause serious respiratory depression.

If concomitant use is necessary, consider increasing the hydrocodone bitartrate and acetaminophen tablets dosage until stable drug effects are achieved [see DOSAGE AND ADMINISTRATION]. Monitor for signs of opioid withdrawal. If a CYP3A4 inducer is discontinued, consider hydrocodone bitartrate and acetaminophen tablets dosage reduction and monitor for signs of respiratory depression.

Central Nervous System Depressants
Due to additive pharmacologic effect, the concomitant use of CNS depressants such as alcohol, benzodiazepines and other sedative hypnotics, anxiolytics, and tranquilizers, muscle relaxants, general anesthetics, antipsychotics, and other opioids, can increase the risk of hypotension, respiratory depression, profound sedation, coma, and death.

Consider dose reduction of one or both drugs. Monitor patients for signs of respiratory depression, sedation, and hypotension [see WARNINGS].

Serotonergic Drugs
The concomitant use of opioids with other drugs that affect the serotonergic neurotransmitter system, such as selective serotonin reuptake inhibitors (SSRIs), serotonin and norepinephrine reuptake inhibitors (SNRIs), tricyclic antidepressants (TCAs), triptans, 5-HT3 receptor antagonists, drugs that effect the serotonin neurotransmitter system (e.g., mirtazapine, trazodone, tramadol), and monoamine oxidase (MAO) inhibitors (those intended to treat psychiatric disorders and also others, such as linezolid and intravenous methylene blue), has resulted in serotonin syndrome. [see PRECAUTIONS;INFORMATION FOR PATIENTS].

If concomitant use is warranted, carefully observe the patient, particularly during treatment initiation and dose adjustment. Discontinue hydrocodone bitartrate and acetaminophen tablets if serotonin syndrome is suspected.

Drug/Laboratory Test Interactions: Acetaminophen may produce false-positive test results for urinary 5-hydroxyindoleacetic acid.

Carcinogenesis, Mutagenesis, Impairment of Fertility

No adequate studies have been conducted in animals to determine whether hydrocodone or acetaminophen have a potential for carcinogenesis, mutagenesis, or impairment of fertility.

Infertility
Chronic use of opioids may cause reduced fertility in females and males of reproductive potential. It is not known whether these effects on fertility are reversible [see ADVERSE REACTIONS].

Pregnancy

Fetal/Neonatal Adverse Reactions
Prolonged use of opioid analgesics during pregnancy for medical or nonmedical purposes can result in physical dependence in the neonate and neonatal opioid withdrawal syndrome shortly after birth.

Neonatal opioid withdrawal syndrome presents as irritability, hyperactivity and abnormal sleep pattern, high pitched cry, tremor, vomiting, diarrhea and failure to gain weight. The onset, duration, and severity of neonatal opioid withdrawal syndrome vary based on the specific opioid used, duration of use, timing and amount of last maternal use, and rate of elimination of the drug by the newborn. Observe newborns for symptoms of neonatal opioid withdrawal syndrome and manage accordingly [seeWARNINGS].

Labor or Delivery
Opioids cross the placenta and may produce respiratory depression and psycho-physiologic effects in neonates. An opioid antagonist, such as naloxone, must be available for reversal of opioid-induced respiratory depression in the neonate. Hydrocodone bitartrate and acetaminophen tablets are not recommended for use in pregnant women during or immediately prior to labor, when other analgesic techniques are more appropriate. Opioid analgesics, including hydrocodone bitartrate and acetaminophen tablets, can prolong labor through actions which temporarily reduce the strength, duration, and frequency of uterine contractions. However, this effect is not consistent and may be offset by an increased rate of cervical dilation, which tends to shorten labor. Monitor neonates exposed to opioid analgesics during labor for signs of excess sedation and respiratory depression.

Nursing Mothers

The developmental and health benefits of breastfeeding should be considered along with the mother’s clinical need for hydrocodone bitartrate and acetaminophen tablets and any potential adverse effects on the breastfed infant from hydrocodone bitartrate and acetaminophen tablets or from the underlying maternal condition.

Infants exposed to hydrocodone bitartrate and acetaminophen through breast milk should be monitored for excess sedation and respiratory depression. Withdrawal symptoms can occur in breastfed infants when maternal administration of an opioid analgesic is stopped, or when breast-feeding is stopped.

Pediatric Use: Safety and effectiveness in pediatric patients have not been established.

Geriatric Use

Elderly patients (aged 65 years or older) may have increased sensitivity to hydrocodone bitartrate and acetaminophen tablets. In general, use caution when selecting a dosage for an elderly patient, usually starting at the low end of the dosing range, reflecting the greater frequency of decreased hepatic, renal, or cardiac function and of concomitant disease or other drug therapy.

Respiratory depression is the chief risk for elderly patients treated with opioids, and has occurred after large initial doses were administered to patients who were not opioid-tolerant or when opioids were co-administered with other agents that depress respiration. Titrate the dosage of hydrocodone bitartrate and acetaminophen tablets slowly in geriatric patients [see WARNINGS].

ADVERSE REACTIONS

The most frequently reported adverse reactions are lightheadedness, dizziness, sedation, nausea, and vomiting. These effects seem to be more prominent in ambulatory than in nonambulatory patients, and some of these adverse reactions may be alleviated if the patient lies down.

Other adverse reactions include:

Central Nervous System: Drowsiness, mental clouding, lethargy, impairment of mental and physical performance, anxiety, fear, dysphoria, psychic dependence, and mood changes.

Gastrointestinal System: Prolonged administration of hydrocodone bitartrate and acetaminophen tablets may produce constipation.

Genitourinary System: Ureteral spasm, spasm of vesical sphincters, and urinary retention have been reported with opiates.

Respiratory Depression: Hydrocodone bitartrate may produce dose-related respiratory depression by acting directly on the brain stem respiratory center (see OVERDOSAGE).

Special Senses: Cases of hearing impairment or permanent loss have been reported predominantly in patients with chronic overdose.

Dermatological: Skin rash, pruritus.

The following adverse drug events may be borne in mind as potential effects of acetaminophen: allergic reactions, rash, thrombocytopenia, agranulocytosis. Potential effects of high dosage are listed in the OVERDOSAGE section.

Postmarketing Experience

serotonin syndrome
adrenal insufficiency

Androgen deficiency
Chronic use of opioids may influence the hypothalamic-pituitary-gonadal axis, leading to androgen deficiency that may manifest as symptoms of hypogonadism, such as impotence, erectile dysfunction, or amenorrhea. The causal role of opioids in the syndrome of hypogonadism is unknown because the various medical, physical, lifestyle, and psychological stressors that may influence gonadal hormone levels have not been adequately controlled for in studies conducted to date. Patients presenting with symptoms of androgen deficiency should undergo laboratory evaluation.

DRUG ABUSE AND DEPENDENCE

Controlled Substance
Hydrocodone bitartrate and acetaminophen tablets contain hydrocodone, a Schedule II controlled substance.

Abuse
Hydrocodone bitartrate and acetaminophen tablets contain hydrocodone, a substance with a high potential for abuse similar to other opioids used in analgesia. Hydrocodone bitartrate and acetaminophen tablets can be abused and is subject to misuse, addiction, and criminal diversion [seeWARNINGS].

All patients treated with opioids require careful monitoring for signs of abuse and addiction, since use of opioid analgesic products carries the risk of addiction even under appropriate medical use.

Prescription drug abuse is the intentional non-therapeutic use of a prescription drug, even once, for its rewarding psychological or physiological effects.

Drug addiction is a cluster of behavioral, cognitive, and physiological phenomena that develop after repeated substance use and includes: a strong desire to take the drug, difficulties in controlling its use, persisting in its use despite harmful consequences, a higher priority given to drug use than to other activities and obligations, increased tolerance, and sometimes a physical withdrawal.

“Drug-seeking” behavior is very common in persons with substance use disorders. Drug-seeking tactics include emergency calls or visits near the end of office hours, refusal to undergo appropriate examination, testing, or referral, repeated “loss” of prescriptions, tampering with prescriptions and reluctance to provide prior medical records or contact information for other treating health care provider(s). “Doctor shopping” (visiting multiple prescribers) to obtain additional prescriptions is common among drug abusers and people suffering from untreated addiction. Preoccupation with achieving adequate pain relief can be appropriate behavior in a patient with poor pain control.

Abuse and addiction are separate and distinct from physical dependence and tolerance. Health care providers should be aware that addiction may not be accompanied by concurrent tolerance and symptoms of physical dependence in all addicts. In addition, abuse of opioids can occur in the absence of true addiction.

Hydrocodone bitartrate and acetaminophen tablets, like other opioids, can be diverted for non-medical use into illicit channels of distribution. Careful record-keeping of prescribing information, including quantity, frequency, and renewal requests, as required by state and federal law, is strongly advised.

Proper assessment of the patient, proper prescribing practices, periodic re-evaluation of therapy, and proper dispensing and storage are appropriate measures that help to limit abuse of opioid drugs.

Risks Specific to Abuse of Hydrocodone Bitartrate and Acetaminophen Tablets
Hydrocodone bitartrate and acetaminophen tablets are for oral use only. Abuse of hydrocodone bitartrate and acetaminophen tablets poses a risk of overdose and death. This risk is increased with concurrent abuse of hydrocodone bitartrate and acetaminophen tablets with alcohol and other substances.

Dependence
Both tolerance and physical dependence can develop during chronic opioid therapy. Tolerance is the need for increasing doses of opioids to maintain a defined effect such as analgesia (in the absence of disease progression or other external factors). Tolerance may occur to both the desired and undesired effects of drugs, and may develop at different rates for different effects.

Physical dependence results in withdrawal symptoms after abrupt discontinuation or a significant dosage reduction of a drug. Withdrawal also may be precipitated through the administration of drugs with opioid antagonist activity (e.g., naloxone, nalmefene), mixed agonist/antagonist analgesics (pentazocine, butorphanol, nalbuphine), or partial agonists (buprenorphine). Physical dependence may not occur to a clinically significant degree until after several days to weeks of continued opioid usage.

Hydrocodone bitartrate and acetaminophen tablets should not be abruptly discontinued [see DOSAGE AND ADMINISTRATION]. If hydrocodone bitartrate and acetaminophen tablets are abruptly discontinued in a physically dependent patient, a withdrawal syndrome may occur. Some or all of the following can characterize this syndrome: restlessness, lacrimation, rhinorrhea, yawning, perspiration, chills, myalgia, and mydriasis. Other signs and symptoms also may develop, including: irritability, anxiety, backache, joint pain, weakness, abdominal cramps, insomnia, nausea, anorexia, vomiting, diarrhea, or increased blood pressure, respiratory rate, or heart rate.

Infants born to mothers physically dependent on opioids will also be physically dependent and may exhibit respiratory difficulties and withdrawal signs [see PRECAUTIONS; PREGNANCY].

OVERDOSAGE

Clinical Presentation
Acute overdose with hydrocodone bitartrate and acetaminophen tablets can be manifested by respiratory depression, somnolence progressing to stupor or coma, skeletal muscle flaccidity, cold and clammy skin, constricted pupils, and, in some cases, pulmonary edema, bradycardia, hypotension, partial or complete airway obstruction, atypical snoring, and death. Marked mydriasis rather than miosis may be seen with hypoxia in overdose situations.

Acetaminophen: In acetaminophen overdosage: dose-dependent, potentially fatal hepatic necrosis is the most serious adverse effect. Renal tubular necrosis, hypoglycemic coma and coagulation defects may also occur. Early symptoms following a potentially hepatotoxic overdose may include: nausea, vomiting, diaphoresis and general malaise. Clinical and laboratory evidence of hepatic toxicity may not be apparent until 48 to 72 hours post-ingestion.

Treatment of Overdose
In case of overdose, priorities are the reestablishment of a patent and protected airway and institution of assisted or controlled ventilation, if needed. Employ other supportive measures (including oxygen and vasopressors) in the management of circulatory shock and pulmonary edema as indicated. Cardiac arrest or arrhythmias will require advanced life-support techniques.

The opioid antagonists, naloxone or nalmefene, are specific antidotes to respiratory depression resulting from opioid overdose. For clinically significant respiratory or circulatory depression secondary to hydrocodone bitartrate and acetaminophen tablets overdose, administer an opioid antagonist. Opioid antagonists should not be administered in the absence of clinically significant respiratory or circulatory depression secondary to hydrocodone bitartrate and acetaminophen tablets overdose.

Because the duration of opioid reversal is expected to be less than the duration of action of hydrocodone bitartrate and acetaminophen in hydrocodone bitartrate and acetaminophen tablets, carefully monitor the patient until spontaneous respiration is reliably re-established. If the response to an opioid antagonist is suboptimal or only brief in nature, administer additional antagonist as directed by the product’s prescribing information.

In an individual physically dependent on opioids, administration of the recommended usual dosage of the antagonist will precipitate an acute withdrawal syndrome. The severity of the withdrawal symptoms experienced will depend on the degree of physical dependence and the dose of the antagonist administered. If a decision is made to treat serious respiratory depression in the physically dependent patient, administration of the antagonist should be begun with care and by titration with smaller than usual doses of the antagonist.

Important Dosage and Administration Instructions
Initiate the dosing regimen for each patient individually, taking into account the patient's severity of pain, patient response, prior analgesic treatment experience, and risk factors for addiction, abuse, and misuse [see WARNINGS].

Monitor patients closely for respiratory depression, especially within the first 24-72 hours of initiating therapy and following dosage increases with hydrocodone bitartrate and acetaminophen tablets and adjust the dosage accordingly [see WARNINGS].

Initial Dosage

Initiating Treatment with Hydrocodone Bitartrate and Acetaminophen Tablets

2.5 mg/325 mg

5 mg/325 mg

The usual adult dosage is one or two tablets every four to six hours as needed for pain.

The total daily dosage should not exceed 8 tablets.

7.5 mg/325 mg

The usual adult dosage is one tablet every four to six hours as needed for pain.

The total daily dosage should not exceed 6 tablets.

10 mg/325 mg

The usual adult dosage is one tablet every four to six hours as needed for pain.

The total daily dosage should not exceed 6 tablets.

Conversion from Other Opioids to Hydrocodone Bitartrate and Acetaminophen Tablets
There is inter-patient variability in the potency of opioid drugs and opioid formulations. Therefore, a conservative approach is advised when determining the total daily dosage of hydrocodone bitartrate and acetaminophen tablets. It is safer to underestimate a patient’s 24-hour hydrocodone bitartrate and acetaminophen tablets dosage than to overestimate the 24-hour hydrocodone bitartrate and acetaminophen tablets dosage and manage an adverse reaction due to overdose.

Titration and Maintenance of Therapy
Individually titrate hydrocodone bitartrate and acetaminophen tablets to a dose that provides adequate analgesia and minimizes adverse reactions. Continually reevaluate patients receiving hydrocodone bitartrate and acetaminophen tablets to assess the maintenance of pain control and the relative incidence of adverse reactions, as well as monitoring for the development of addiction, abuse, or misuse [see WARNINGS]. Frequent communication is important among the prescriber, other members of the healthcare team, the patient, and the caregiver/family during periods of changing analgesic requirements, including initial titration.

If the level of pain increases after dosage stabilization, attempt to identify the source of increased pain before increasing the hydrocodone bitartrate and acetaminophen tablets dosage. If unacceptable opioid-related adverse reactions are observed, consider reducing the dosage. Adjust the dosage to obtain an appropriate balance between management of pain and opioid-related adverse reactions.

Discontinuation of Hydrocodone Bitartrate and Acetaminophen Tablets
When a patient who has been taking hydrocodone bitartrate and acetaminophen tablets regularly and may be physically dependent no longer requires therapy with hydrocodone bitartrate and acetaminophen tablets, use a gradual downward titration of the dosage to prevent signs and symptoms of withdrawal. Do not stop hydrocodone bitartrate and acetaminophen tablets abruptly [seeWARNINGS, DRUG ABUSE AND DEPENDENCE].

Medication Guide

Hydrocodone Bitartrate and Acetaminophen
(hye” droe koe’ done bye tar’ trate and a seet” a min’ oh fen)
Tablets, USP, CII

Hydrocodone bitartrate and acetaminophen tablets are:

A strong prescription pain medicine that contains an opioid (narcotic) that is used to manage moderate to moderately severe pain, when other pain treatments such as non-opioid pain medicines do not treat your pain well enough or you cannot tolerate them.
An opioid pain medicine that can put you at risk for overdose and death. Even if you take your dose correctly as prescribed you are at risk for opioid addiction, abuse, and misuse that can lead to death.

Important information about hydrocodone bitartrate and acetaminophen tablets:

Get emergency help right away if you take too much hydrocodone bitartrate and acetaminophen tablets (overdose). When you first start taking hydrocodone bitartrate and acetaminophen tablets, when your dose is changed, or if you take too much (overdose), serious or life-threatening breathing problems that can lead to death may occur.
Never give anyone else your hydrocodone bitartrate and acetaminophen tablets. They could die from taking them. Store hydrocodone bitartrate and acetaminophen tablets away from children and in a safe place to prevent stealing or abuse. Selling or giving away hydrocodone bitartrate and acetaminophen tablets is against the law.

Do not take hydrocodone bitartrate and acetaminophen tablets if you have:

severe asthma, trouble breathing, or other lung problems.
a bowel blockage or have narrowing of the stomach or intestines.
signs or allergy such as a rash.
are allergic to any of its ingredients.

Before taking hydrocodone bitartrate and acetaminophen tablets, tell your healthcare provider if you have a history of:

head injury, seizures ● liver, kidney, thyroid problems
problems urinating ● pancreas or gallbladder problems
abuse of street or prescription drugs, alcohol addiction, or mental health problems.

Tell your healthcare provider if you are:

pregnant or planning to become pregnant. Prolonged use of hydrocodone bitartrate and acetaminophen tablets during pregnancy can cause withdrawal symptoms in your newborn baby that could be life-threatening if not recognized and treated.
breastfeeding. Hydrocodone bitartrate and acetaminophen passes into breast milk and may harm your baby.
taking prescription or over-the-counter medicines, vitamins, or herbal supplements. Taking hydrocodone bitartrate and acetaminophen tablets with certain other medicines can cause serious side effects that could lead to death.

When taking hydrocodone bitartrate and acetaminophen tablets:

Do not change your dose. Take hydrocodone bitartrate and acetaminophen tablets exactly as prescribed by your healthcare provider.
Take your prescribed dose every four to six hours at the same time every day. Do not take more than your prescribed dose. If you miss a dose, take your next dose at your usual time.
Call your healthcare provider if the dose you are taking does not control your pain.
If you have been taking hydrocodone bitartrate and acetaminophen tablets regularly, do not stop taking hydrocodone bitartrate and acetaminophen tablets without talking to your healthcare provider.
After you stop taking hydrocodone bitartrate and acetaminophen tablets, flush any unused tablets down the toilet.

While taking hydrocodone bitartrate and acetaminophen tablets DO NOT:

Drive or operate heavy machinery, until you know how hydrocodone bitartrate and acetaminophen tablets affects you. Hydrocodone bitartrate and acetaminophen tablets can make you sleepy, dizzy, or lightheaded.
Drink alcohol or use prescription or over-the-counter medicines that contain alcohol. Using products containing alcohol during treatment with hydrocodone bitartrate and acetaminophen tablets may cause you to overdose and die.

The possible side effects of hydrocodone bitartrate and acetaminophen tablets:

constipation, nausea, sleepiness, vomiting, tiredness, headache, dizziness, abdominal pain. Call your healthcare provider if you have any of these symptoms and they are severe.

Get emergency medical help if you have:

trouble breathing, shortness of breath, fast heartbeat, chest pain, swelling of your face, tongue, or throat, extreme drowsiness, light-headedness when changing positions, feeling faint, agitation, high body temperature, trouble walking, stiff muscles, or mental changes such as confusion.

These are not all the possible side effects of hydrocodone bitartrate and acetaminophen tablets. Call your doctor for medical advice about side effects.

You may report side effects to FDA at 1-800-FDA-1088.

For more information go to dailymed.nlm.nih.gov

This Medication Guide has been approved by the U.S. Food and Drug Administration.